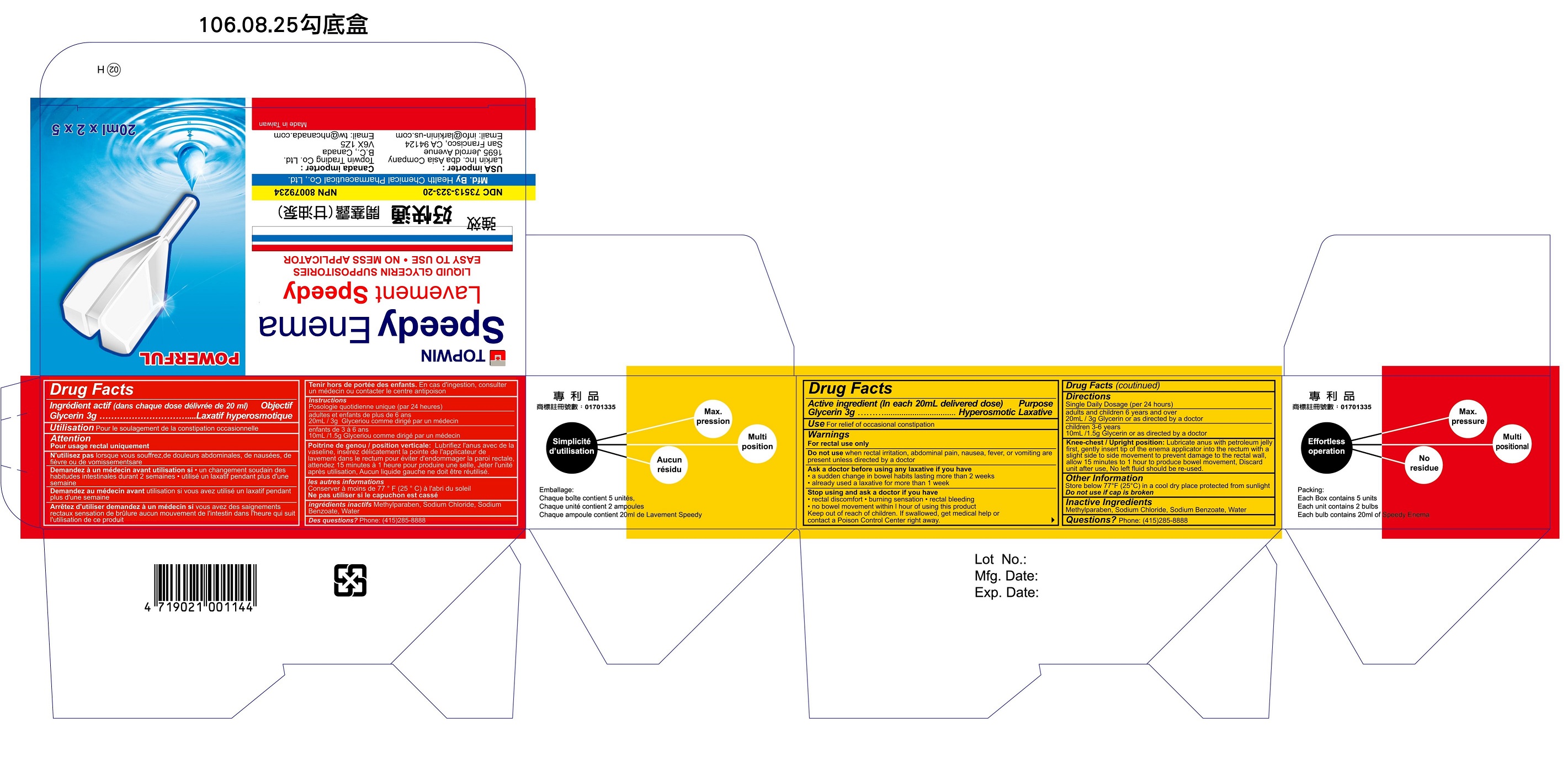 DRUG LABEL: Topwin Speedy Enema
NDC: 73513-323 | Form: ENEMA
Manufacturer: Health Chemical Pharmaceutical Co., Ltd
Category: otc | Type: HUMAN OTC DRUG LABEL
Date: 20251128

ACTIVE INGREDIENTS: GLYCERIN 3 g/100 mL
INACTIVE INGREDIENTS: METHYLPARABEN; SODIUM CHLORIDE; SODIUM BENZOATE; WATER

Health Chemical Pharmaceutical Co., Ltd

Active Ingredient

Glycerin 3g

Purpose

Glycerin Hyperosmotic Laxative

Uses

For relief of occasional constipation

Warnings

For rectal use only

Do not use

when rectal irritation, abdominal pain, nausea, fever, or vomiting are present unless directed by a doctor.

Ask a doctor before using any laxative if you have

- a sudden change in bowel habits lasting more than 2 weeks
- already used a laxative for more than 1 week

Stop using and ask a doctor if you have

- rectal discomfort
- burning sensation
- rectal bleeding
- no bowel movement within 1 hour of using this product

Keep out of reach of children

If swallowed, get medical help or contact a Poison Control Center right away.

Directions

- Single Daily Usage (per 24 hours)
- Adults and children, 6 years and over: 20 ml / 3g Glycerin or as directed by a doctor
- Children 3-6 years: 10 ml / 1.5g Glycerin or as directed by a doctor
- Knee-chest / Upright position: Lubricate anus with petroleum jelly first, gently insert tip of the enema applicator into the rectum with a single side to side movement to prevent damage to the rectal wall, allow 15 minutes to 1 hour to produce bowel movement. Discard unit after use. No left fluid should be re-used.

Other Information

Store below 77°F (25 °C) in a cool dry place and protected from sunlight. Do not use if cap is broken.

Inactive Ingredients

Methylparaben, Sodium Chloride, Sodium Benzoate, Water

Questions?

Manufactured by Health Chemical Pharmaceutical Co, Ltd
Made in Taiwan

U.S. Importer: Larkin Inc. dba Asia Company
1695 Jerrold Avenue, San Francisco, CA 94124
Email: info@larkinin-us.com
Phone: (415)285-8888